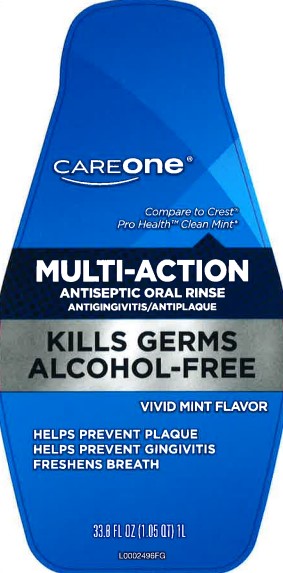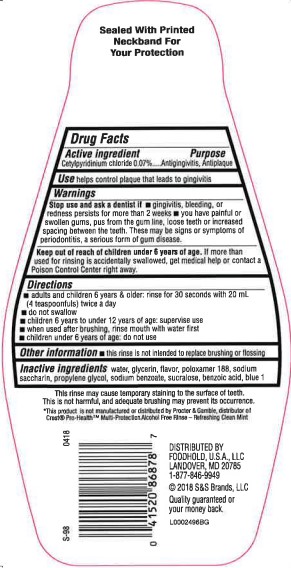 DRUG LABEL: Multi-Action Antiseptic
NDC: 41520-299 | Form: RINSE
Manufacturer: American Sales Company
Category: otc | Type: HUMAN OTC DRUG LABEL
Date: 20260206

ACTIVE INGREDIENTS: CETYLPYRIDINIUM CHLORIDE 0.7 mg/1 mL
INACTIVE INGREDIENTS: WATER; GLYCERIN; POLOXAMER 188; SACCHARIN SODIUM; PROPYLENE GLYCOL; SODIUM BENZOATE; SUCRALOSE; BENZOIC ACID; FD&C BLUE NO. 1

Care One 299.005/299AK-AL
Multi-Action Alcohol-free antiseptic Mouth Rinse with CPC

TEP

Sealed With Printed Neckband For Your Protection

Active ingredient

Cetylpyridinium Chloride 0.07%

Purpose

Antigingivitis, Antiplaque

Use

helps control plaque that leads to gingivitis

Warnings

for this product

Stop use and ask a dentist if

- gingivitis, bleeding or redness persists for more than 2 weeks
- you have painful or swollen gums, pus from the gum line, loose teeth or increased spacing between the teeth. These may be signs or symptoms of periodontitis, a serious form of gum disease.

Keep out of reach of children under 6 years of age.

If more than used for rinsing is accidentally swallowed, get medical help or contact a Poison Control center right away.

Directions

- adults and children 6 years & older: rinse for 30 seconds with 20 mL (4 teaspoonfuls) twice a day
- do not swallow
- children 6 years to under 12 years of age: supervise use
- when used after brushing, rinse mouth with water first
- children under 6 years of age: do not use

Other information

- this rinse is not intended to replace brushing or flossing

Inactive ingredients

water, glycerin, flavor, poloxamer 188, sodium saccharin, propylene glycol, sodium benzoate, sucralose, benzoic acid, blue 1

Disclaimer

This rinse may cause temporary staining to the surface of teeth. This is not harmful, and adequate brushing may prevent its occurence

*This product is not manufactured or distributed by Proctor & Gamble, distributer of Crest Pro-Health Multi-Protection Alcohol Free Rinse - Refreshing Clean Mint

ADVERSE REACTION

DISTRIBUTED BY:

Foodhold U.S.A., LLC

Landover, MD 20785

1-877-846-9949

(c) 2018 S&S Brands, LLC

Quality guaranteed or your money back

principal display panel

CAREONE

*Compare to Crest Pro Health Clean Mint*

MULTI-ACTION

ANTISEPTIC ORAL RINSE

ANTIGINGIVITIS/ANTIPLAQUE

KILLS GERMS

ALCOHOL-FREE

VIVID MINT FLAVOR

HELPS PREVENT PLAQUE

HELPS PREVENT GINGIVITIIS

FRESHENS BREATH

33.8 FL OZ (1.05 QT) 1 L